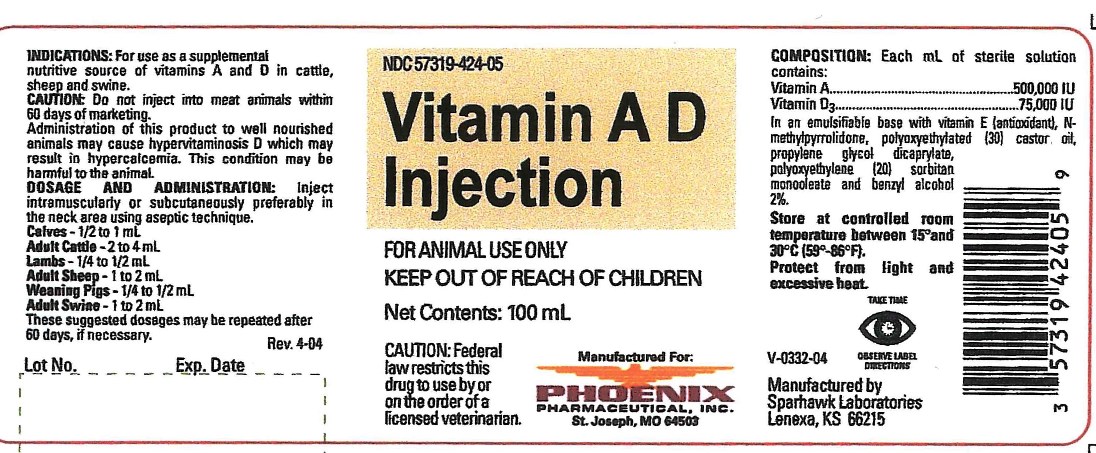 DRUG LABEL: VITAMIN AD
NDC: 57319-424 | Form: INJECTION
Manufacturer: Phoenix Pharmaceutical Inc
Category: animal | Type: OTC ANIMAL DRUG LABEL
Date: 20181023

ACTIVE INGREDIENTS: RETINOL 500000 [iU]/1 mL; CHOLECALCIFEROL 75000 [iU]/1 mL

VITAMIN AD INJECTION

INDICATIONS AND USAGE

FOR ANIMAL USE ONLY

KEEP OUT OF REACH OF CHILDREN

CAUTION: Federal law restricts this drug to use by or on the order of a licensed veterinarian.

INDICATIONS

For use as a supplemental nutritive source of vitamins A and D in cattle, sheep and swine.

CAUTION

Do not inject into meat animals within 60 days of marketing.

Administration of this product to well nourished animals may cause hypervitaminosis D which may result in hypercalcemia. This condition may be harmful to the animal.

DOSAGE AND ADMINISTRATION

Inject intramuscularly or subcutaneously preferably in the neck area using aseptic technique.

Calves - 1/2 to 1 mL

Adult Cattle - 2 to 4 mL

Lambs - 1/4 to 1/2 mL

Adult Sheep - 1 to 2 mL

Weaning Pigs - 1/4 to 1/2 mL

Adult Swine - 1 to 2 mL

These suggested dosage may be repeated after 60 days, if necessary.

TAKE TIME OBSERVE LABEL DIRECTIONS

COMPOSITION

Each mL of sterile solution contains:
Vitamin A . . . . . . . . . 500,000 IU
Vitamin D3 . . . . . . . . . 75,000 IU
In an emulsifiable base with vitamin E (antioxidant), N-methylpyrrolidone, polyoxyethylated (30) castor oil, propylene glycol dicaprylate, polyoxyethylene (20) sorbitan monooleate and benzyl alcohol 2%.

STORAGE

Store at controlled room temperature between 15o and 30oC (59-86oF).

Protect from light and excessive heat.